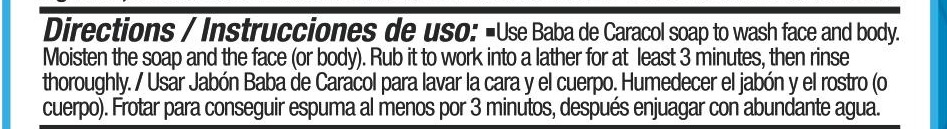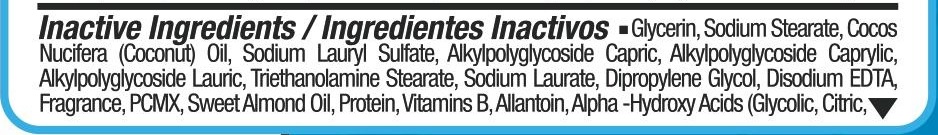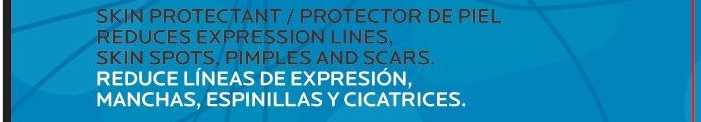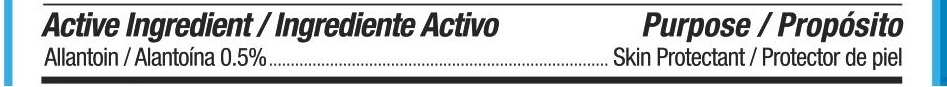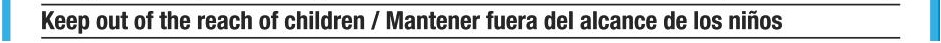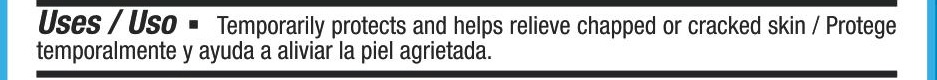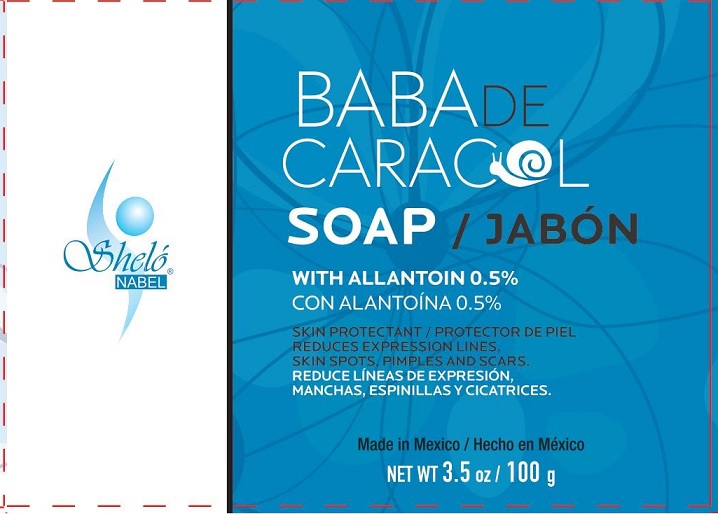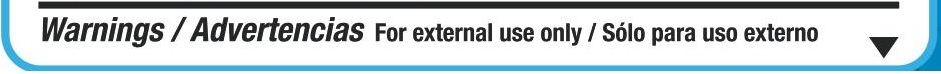 DRUG LABEL: Shelo NABEL Jabon Baba Car
NDC: 71424-1161 | Form: SOAP
Manufacturer: Corporativo Serysi S de R L de C V
Category: otc | Type: HUMAN OTC DRUG LABEL
Date: 20170523

ACTIVE INGREDIENTS: ALLANTOIN 5 mg/1 g
INACTIVE INGREDIENTS: GLYCERIN

Sheló NABEL Jabón Baba de Caracol